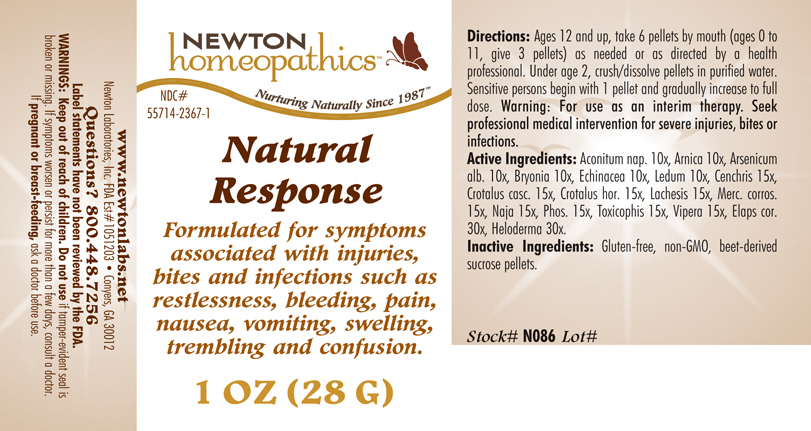 DRUG LABEL: Natural Response 
NDC: 55714-2367 | Form: PELLET
Manufacturer: Newton Laboratories, Inc.
Category: homeopathic | Type: HUMAN OTC DRUG LABEL
Date: 20141110

ACTIVE INGREDIENTS: Aconitum Napellus 10 [hp_X]/1 g; Arnica Montana 10 [hp_X]/1 g; Arsenic Trioxide 10 [hp_X]/1 g; Bryonia Alba Root 10 [hp_X]/1 g; Echinacea, Unspecified 10 [hp_X]/1 g; Ledum Palustre Twig 10 [hp_X]/1 g; Agkistrodon Contortrix Venom 15 [hp_X]/1 g; Crotalus Durissus Terrificus Venom 15 [hp_X]/1 g; Crotalus Horridus Horridus Venom 15 [hp_X]/1 g; Lachesis Muta Venom 15 [hp_X]/1 g; Mercuric Chloride 15 [hp_X]/1 g; Naja Naja Venom 15 [hp_X]/1 g; Phosphorus 15 [hp_X]/1 g; Agkistrodon Piscivorus Venom 15 [hp_X]/1 g; Vipera Berus Venom 15 [hp_X]/1 g; Micrurus Corallinus Venom 30 [hp_X]/1 g; Heloderma Suspectum Venom 30 [hp_X]/1 g
INACTIVE INGREDIENTS: Sucrose

Natural Response

INDICATIONS & USAGE SECTION

Formulated for symptoms associated with injuries, bites and infections such as restlessness, bleeding, pain, nausea, vomiting, swelling, trembling and confusion.

DOSAGE & ADMINISTRATION SECTION

Directions: Ages 12 and up, take 6 pellets by mouth (ages 0 to 11, give 3 pellets) as needed or as directed by a health professional. Under age 2, crush/dissolve pellets in purified water. Sensitive persons begin with 1 pellet and gradually increase to full dose. Warning: For use as an interim therapy. Seek professional medical intervention for severe injuries, bites or infections.

OTC - ACTIVE INGREDIENT SECTION

Aconitum nap. 10x, Arnica 10x, Arsenicum alb. 10x, Bryonia 10x, Echinacea 10x, Ledum 10x, Cenchris 15x, Crotalus casc. 15x, Crotalus hor. 15x, Lachesis 15x, Merc. corros. 15x, Naja 15x, Phos. 15x, Toxicophis 15x, Vipera 15x, Elaps cor. 30x, Heloderma 30x.

OTC - PURPOSE SECTION

Formulated for symptoms associated with injuries, bites and infections such as restlessness, bleeding, pain, nausea, vomiting, swelling, trembling and confusion.

INACTIVE INGREDIENT SECTION

Inactive Ingredients: Gluten-free, non-GMO, beet-derived sucrose pellets.

QUESTIONS SECTION

www.newtonlabs.net Newton Laboratories, Inc. FDA Est # 1051203 - Conyers, GA 30012
Questions? 1.800.448.7256

WARNINGS SECTION

Warning: Keep out of reach of children. Do not use if tamper-evident seal is broken or missing. If symptoms worsen or persist for more than a few days, consult a doctor. If pregnant or breast-feeding, ask a doctor before use.

OTC - PREGNANCY OR BREAST FEEDING SECTION

If pregnant or breast-feeding, ask a doctor before use.

OTC - KEEP OUT OF REACH OF CHILDREN SECTION

Keep out of reach of children.